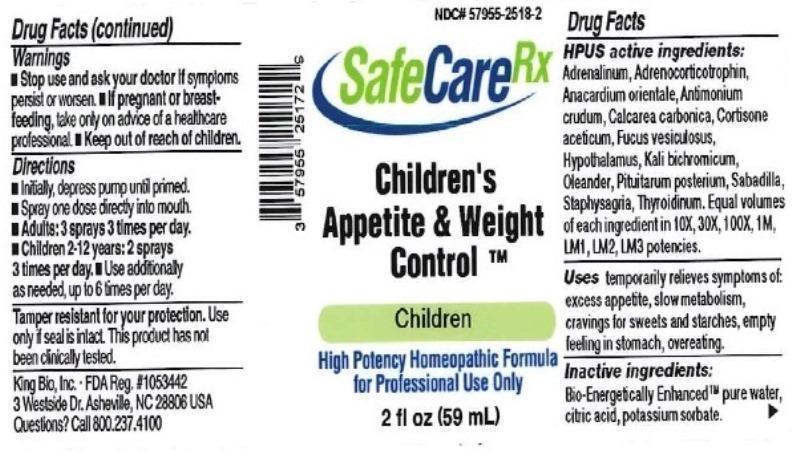 DRUG LABEL: Childrens Appetite and Weight Control
NDC: 57955-2518 | Form: LIQUID
Manufacturer: King Bio Inc.
Category: homeopathic | Type: HUMAN OTC DRUG LABEL
Date: 20150831

ACTIVE INGREDIENTS: CORTICOTROPIN 10 [hp_X]/59 mL; EPINEPHRINE 10 [hp_X]/59 mL; SEMECARPUS ANACARDIUM JUICE 10 [hp_X]/59 mL; ANTIMONY TRISULFIDE 10 [hp_X]/59 mL; OYSTER SHELL CALCIUM CARBONATE, CRUDE 10 [hp_X]/59 mL; CORTISONE ACETATE 10 [hp_X]/59 mL; FUCUS VESICULOSUS 10 [hp_X]/59 mL; BOS TAURUS HYPOTHALAMUS 10 [hp_X]/59 mL; POTASSIUM DICHROMATE 10 [hp_X]/59 mL; NERIUM OLEANDER LEAF 10 [hp_X]/59 mL; SUS SCROFA PITUITARY GLAND 10 [hp_X]/59 mL; SCHOENOCAULON OFFICINALE SEED 10 [hp_X]/59 mL; DELPHINIUM STAPHISAGRIA SEED 10 1/59 mL; THYROID, UNSPECIFIED 10 [hp_X]/59 mL
INACTIVE INGREDIENTS: WATER; ANHYDROUS CITRIC ACID; POTASSIUM SORBATE

Children's Appetite and Weight Control™

ACTIVE INGREDIENT

Drug Facts__________________________________________________________________________________________________________

HPUS active ingredients: Adrenocorticotrophin, Adrenalinum, Anacardium orientale, Antimonium crudum, Calcarea carbonica, Cortisone aceticum, Fucus vesiculosus, Hypothalamus, Kali bichromicum, Oleander, Pituitarum posterium, Sabadilla, Staphysagria, Thyroidinum. Equal volumes of each ingredient in 10X, 30X, 100X, 1M, LM1, LM2, LM3 potencies.

INDICATIONS AND USAGE

Uses temporarily relieves symptoms of: excess appetite, slow metabolism, cravings for sweets and starches, empty feeling in stomach, overeating.

Inactive Ingredients:

Bio-Energetically Enhanced™ pure water, citric acid and potassium sorbate.

Warnings

- Stop use and ask your doctor if symptoms persist or worsen.
- If pregnant or breast-feeding, take only on advice of a healthcare professional.

- Keep out of reach of children.

Directions

- Initially, depress pump until primed.
- Spray one dose directly into mouth.
- Adults 12 and up: 3 sprays 3 times per day.
- Children 2-12: 2 sprays 3 times per day.
- Use additionally as needed, up to 6 times per day.

OTHER SAFETY INFORMATION

Tamper resistant for your protection. Use only if safety seal is intact. This product has not been clinically tested.

PURPOSE

Uses temporary relieves symptoms of:

- excess appetite
- slow metabolism
- cravings for sweets and starches
- empty feeling in stomach
- overeating